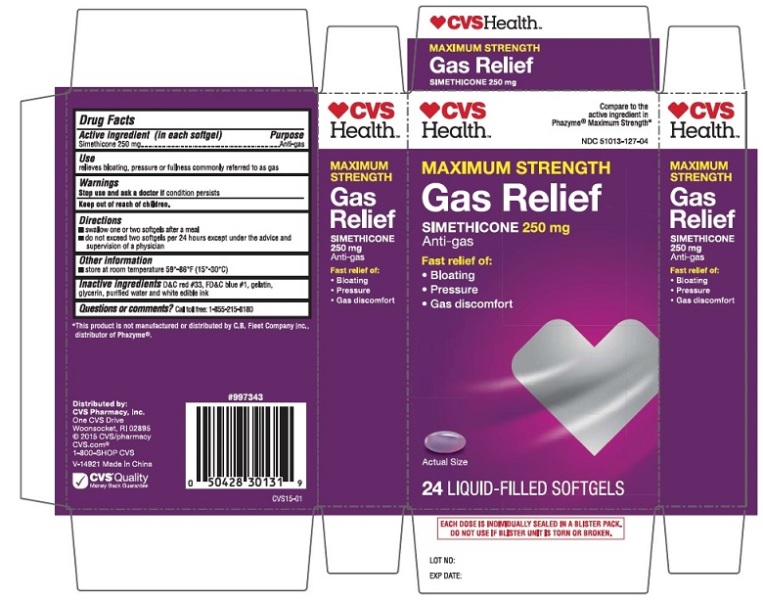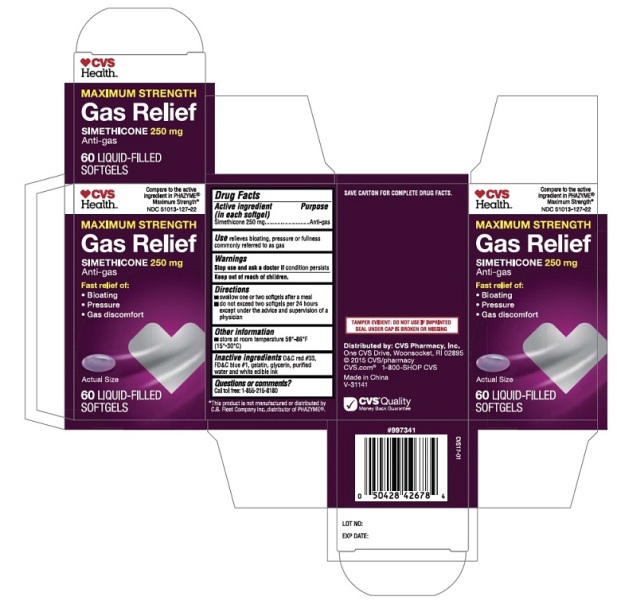 DRUG LABEL: Maximum Strength Gas Relief
NDC: 51013-127 | Form: CAPSULE, LIQUID FILLED
Manufacturer: PURACAP PHARMACEUTICAL LLC
Category: otc | Type: HUMAN OTC DRUG LABEL
Date: 20191220

ACTIVE INGREDIENTS: DIMETHICONE 250 mg/1 1
INACTIVE INGREDIENTS: D&C RED NO. 33; FD&C BLUE NO. 1; GELATIN; GLYCERIN; WATER

SIMETHICONE CAPSULES 250 mg, liquid filled

Active ingredient (in each softgel)

Simethicone 250 mg

Purpose

Anti-gas

Use

- relieves bloating, pressure or fullness commonly referred to as gas

Warnings

Stop use and ask a doctor if

condition persists

Keep out of reach of children.

Directions

- swallow one or two softgels after a meal
- do not exceed two softgels per 24 hours except under the advice and supervision of a physician

Other information

- store at room temperature 59°-86°F (15°-30°C)

Inactive ingredients

D&C red #33, FD&C blue #1, gelatin, glycerin, purified water, and white edible ink

Questions or Comments?

Call: 1-855-215-8180

PRINCIPAL DISPLAY PANEL - 24ct

CVS MAXIMUM STRENGTH GAS RELIEF Anti-gas

SIMETHICONE 250 mg

NDC 51013-127-04

Compare to the active ingredient in PHAZYME® Maximum Strength

24 Liquid-Filled SoftGels

PRINCIPAL DISPLAY PANEL - 60ct

CVS MAXIMUM STRENGTH GAS RELIEF Anti-gas

SIMETHICONE 250 mg

NDC 51013-127-22

Compare to the active ingredient in PHAZYME® Maximum Strength

60 Liquid-Filled SoftGels